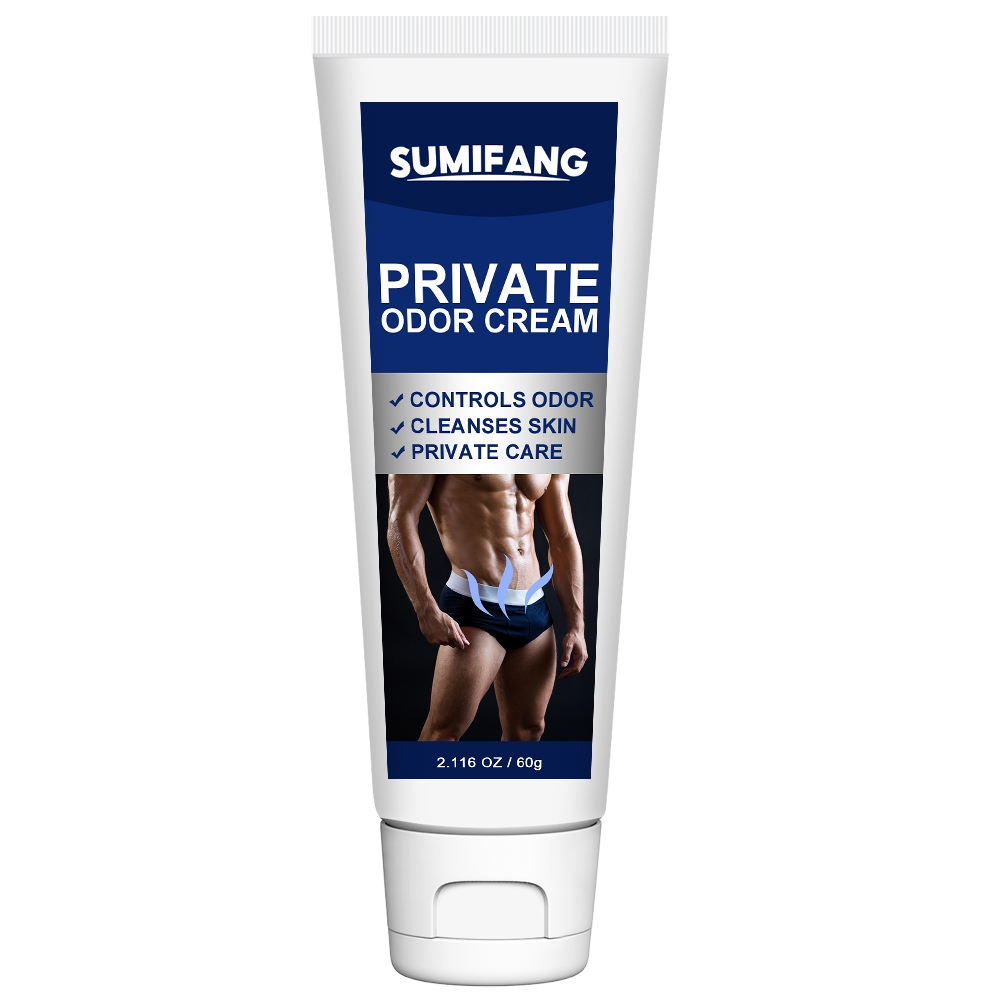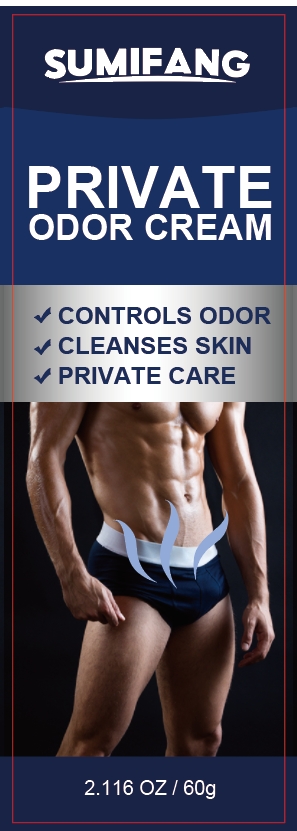 DRUG LABEL: PRIVATE ODORCREAM
NDC: 84025-155 | Form: CREAM
Manufacturer: Guangzhou Yanxi Biotechnology Co.. Ltd
Category: otc | Type: HUMAN OTC DRUG LABEL
Date: 20240817

ACTIVE INGREDIENTS: HYALURONIC ACID 5 mg/60 g; GLYCERIN 3 mg/60 g
INACTIVE INGREDIENTS: WATER

DOSAGE AND ADMINISTRATION

Body lotion for cleaning the skin and solving the problem of greasy skin

WARNINGS

Keep out of children

INACTIVE INGREDIENT

Aqua

INDICATIONS AND USAGE

For men's daily skin care

Keep out of children

PURPOSE

Effectively cleans the private skin and controls men's skin odor